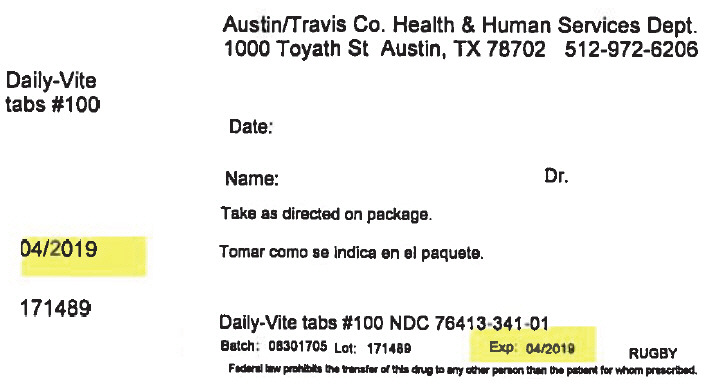 DRUG LABEL: Daily-Vite
NDC: 76413-341 | Form: TABLET
Manufacturer: Central Texas Community Health Centers
Category: other | Type: DIETARY SUPPLEMENT
Date: 20170922

ACTIVE INGREDIENTS: VITAMIN A ACETATE 5000 [iU]/1 1; ASCORBIC ACID 60 mg/1 1; CHOLECALCIFEROL 400 [iU]/1 1; THIAMINE HYDROCHLORIDE 1.5 mg/1 1; RIBOFLAVIN 1.7 mg/1 1; NIACIN 20 mg/1 1; PYRIDOXINE HYDROCHLORIDE 2 mg/1 1; Folic acid 0.4 mg/1 1; CYANOCOBALAMIN 6 ug/1 1
INACTIVE INGREDIENTS: ANHYDROUS DIBASIC CALCIUM PHOSPHATE; stearic acid; microcrystalline cellulose; HYPROMELLOSE, UNSPECIFIED; talc; GELATIN, UNSPECIFIED; croscarmellose sodium; sucrose; FD&C RED NO. 40; ALUMINUM OXIDE; mineral oil; POLYETHYLENE GLYCOL, UNSPECIFIED; titanium dioxide; sodium ascorbate; triacetin; FD&C YELLOW NO. 6; SILICON DIOXIDE; TOCOPHEROL; BUTYLATED HYDROXYTOLUENE

Daily-Vite

SAFE HANDLING WARNING

TAMPER RESISTANT - DO NOT USE IF IMPRINTED SAFETY SEAL UNDER CAP IS BROKEN OR MISSING

DIRECTIONS

Adults only: One tablet daily, preferably with a meal, as a dietary supplement or as directed by your doctor.

STATEMENT OF IDENTITY

Supplement Facts
Serving Size 1 Tablet
Amount per tablet |  | % Daily Value
Vitamin A (as acetate) | 5000 IU | 100%
Vitamin C (as ascorbic acid) | 60 mg | 100%
Vitamin D-3 (as cholecalciferol) | 400 IU | 100%
Vitamin B-1 (as thiamine HCl) | 1.5 mg | 100%
Vitamin B-2 (riboflavin) | 1.7 mg | 100%
Niacin (as Vitamin B-3) | 20 mg | 100%
Vitamin B-6 (as pyridoxine HCl) | 2 mg | 100%
Folic Acid | 0.4 mg | 100%
Vitamin B-12 (as cyanocobalamin) | 6 mcg | 100%

Other Ingredients: Dicalcium phosphate, stearic acid, microcrystalline cellulose, starch, hypromellose, talc, gelatin, croscarmellose sodium, sucrose, FD&C red #40 lake, mineral oil, polyethylene glycol, titanium dioxide, sodium ascorbate, triglycerides, triacetin, FD&C yellow #6 lake, silica, mixed tocopherols and BHT.

HEALTH CLAIM

To preserve quality and freshness, keep bottle tightly closed.

Store between 15° - 30°C (59° - 86°F).

KEEP OUT OF REACH OF CHILDREN.

Questions or comments?
1-800-645-2158
www.rugbylaboratories.com

Distributed by:
Rugby Laboratories
31778 Enterprise Drive
Livonia, MI 48150

Re-order No. 370496
Rev. 03/16 R-29
11087-03-16

LOT # / EXP. DATE:

PRINCIPAL DISPLAY PANEL - 100 Tablet Bottle Label

Austin/Travis Co. Health & Human Services Dept.
1000 Toyath St Austin, TX 78702 512-972-6206

Daily-Vite
tabs #100

Date:

Name:
Dr.

Take as directed on package.

04/2019

171489

Daily-Vite tabs #100 NDC 76413-341-01

Batch:
08301705
Lot:
171489
Exp:
04/2019

RUGBY

Federal law prohibits the transfer of this drug to any other person than the patient for whom prescribed.